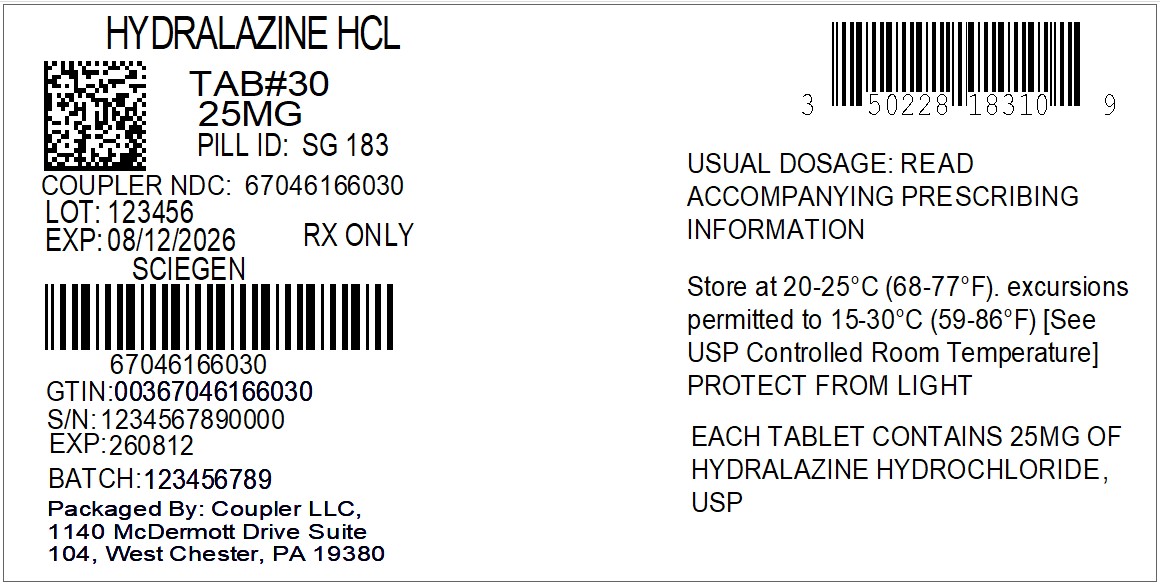 DRUG LABEL: Hydralazine Hydrochloride
NDC: 67046-1660 | Form: TABLET
Manufacturer: Coupler LLC
Category: prescription | Type: HUMAN PRESCRIPTION DRUG LABEL
Date: 20260212

ACTIVE INGREDIENTS: HYDRALAZINE HYDROCHLORIDE 25 mg/1 1
INACTIVE INGREDIENTS: ANHYDROUS LACTOSE; FD&C YELLOW NO. 6; MICROCRYSTALLINE CELLULOSE; SODIUM STARCH GLYCOLATE TYPE A POTATO; STEARIC ACID

HydrALAZINE Hydrochloride
Tablets USP

DESCRIPTION

Hydralazine Hydrochloride tablets USP, is an antihypertensive, for oral administration. Its chemical name is 1-hydrazinophthalazine monohydrochloride, and its structural formula is:

C8H8N4.HCl M.W. 196.64

Hydralazine Hydrochloride USP is a white to off-white, odorless crystalline powder. It is soluble in water, slightly soluble in alcohol. It melts at about 275°C, with decomposition.
Each tablet for oral administration contains 10 mg, 25 mg, 50 mg or 100 mg hydralazine hydrochloride, USP. Tablets also contain anhydrous lactose, FD&C yellow no. 6 aluminum lake, microcrystalline cellulose, sodium starch glycolate, and stearic acid.

CLINICAL PHARMACOLOGY

Although the precise mechanism of action of hydralazine is not fully understood, the major effects are on the cardiovascular system.

Hydralazine apparently lowers blood pressure by exerting a peripheral vasodilating effect through a direct relaxation of vascular smooth muscle. Hydralazine, by altering cellular calcium metabolism, interferes with the calcium movements within the vascular smooth muscle that are responsible for initiating or maintaining the contractile state.

The peripheral vasodilating effect of hydralazine results in decreased arterial blood pressure (diastolic more than systolic); decreased peripheral vascular resistance; and an increased heart rate, stroke volume, and cardiac output. The preferential dilatation of arterioles, as compared to veins, minimizes postural hypotension and promotes the increase in cardiac output. Hydralazine usually increases renin activity in plasma, presumably as a result of increased secretion of renin by the renal juxtaglomerular cells in response to reflex sympathetic discharge. This increase in renin activity leads to the production of angiotensin II, which then causes stimulation of aldosterone and consequent sodium reabsorption. Hydralazine also maintains or increases renal and cerebral blood flow.

Hydralazine is rapidly absorbed after oral administration, and peak plasma levels are reached at 1 to 2 hours. Plasma levels of apparent hydralazine decline with a half-life of 3 to 7 hours. Binding to human plasma protein is 87%. Plasma levels of hydralazine vary widely among individuals. Hydralazine is subject to polymorphic acetylation; slow acetylators generally have higher plasma levels of hydralazine and require lower doses to maintain control of blood pressure. Hydralazine undergoes extensive hepatic metabolism; it is excreted mainly in the form of metabolites in the urine.

INDICATIONS AND USAGE

Essential hypertension, alone or as an adjunct.

CONTRAINDICATIONS

Hypersensitivity to hydralazine; coronary artery disease; mitral valvular rheumatic heart disease.

WARNINGS

In a few patients hydralazine may produce a clinical picture simulating systemic lupus erythematosus including glomerulonephritis. In such patients hydralazine should be discontinued unless the benefit-to-risk determination requires continued antihypertensive therapy with this drug. Symptoms and signs usually regress when the drug is discontinued but residua have been detected many years later.
Long-term treatment with steroids may be necessary. (See PRECAUTIONS, Laboratory Tests.)

PRECAUTIONS

General

Myocardial stimulation produced by hydralazine can cause anginal attacks and ECG changes of myocardial ischemia. The drug has been implicated in the production of myocardial infarction. It must, therefore, be used with caution in patients with suspected coronary artery disease.

The “hyperdynamic” circulation caused by hydralazine may accentuate specific cardiovascular inadequacies. For example, hydralazine may increase pulmonary artery pressure in patients with mitral valvular disease. The drug may reduce the pressor responses to epinephrine. Postural hypotension may result from hydralazine but is less common than with ganglionic blocking agents. It should be used with caution in patients with cerebral vascular accidents.

In hypertensive patients with normal kidneys who are treated with hydralazine, there is evidence of increased renal blood flow and a maintenance of glomerular filtration rate. In some instances where control values were below normal, improved renal function has been noted after administration of hydralazine. However, as with any antihypertensive agent, hydralazine should be used with caution in patients with advanced renal damage.

Peripheral neuritis, evidenced by paresthesia, numbness, and tingling, has been observed. Published evidence suggests an antipyridoxine effect, and that pyridoxine should be added to the regimen if symptoms develop.

Information for Patients

Patients should be informed of possible side effects and advised to take the medication regularly and continuously as directed.

Laboratory Tests

Complete blood counts and antinuclear antibody titer determinations are indicated before and periodically during prolonged therapy with hydralazine even though the patient is asymptomatic. These studies are also indicated if the patient develops arthralgia, fever, chest pain, continued malaise, or other unexplained signs or symptoms.

A positive antinuclear antibody titer requires that the physician carefully weigh the implications of the test results against the benefits to be derived from antihypertensive therapy with hydralazine.

Blood dyscrasias, consisting of reduction in hemoglobin and red cell count, leukopenia, agranulocytosis, and purpura, have been reported. If such abnormalities develop, therapy should be discontinued.

Drug/Drug Interactions

MAO inhibitors should be used with caution in patients receiving hydralazine.
When other potent parenteral antihypertensive drugs, such as diazoxide, are used in combination with hydralazine, patients should be continuously observed for several hours for any excessive fall in blood pressure. Profound hypotensive episodes may occur when diazoxide injection and hydralazine are used concomitantly.

Drug/Food Interactions

Administration of hydralazine with food results in higher plasma levels.

Carcinogenesis, Mutagenesis, Impairment of Fertility

In a lifetime study in Swiss albino mice, there was a statistically significant increase in the incidence of lung tumors (adenomas and adenocarcinomas) of both male and female mice given hydralazine continuously in their drinking water at a dosage of about 250 mg/kg per day (about 80 times the maximum recommended human dose). In a 2-year carcinogenicity study of rats given hydralazine by gavage at dose levels of 15, 30, and 60 mg/kg/day (approximately 5 to 20 times the recommended human daily dosage), microscopic examination of the liver revealed a small, but statistically significant, increase in benign neoplastic nodules in male and female rats from the high-dose group and in female rats from the intermediate-dose group. Benign interstitial cell tumors of the testes were also significantly increased in male rats from the high-dose group. The tumors observed are common in aged rats and a significantly increased incidence was not observed until 18 months of treatment. Hydralazine was shown to be mutagenic in bacterial systems (Gene Mutation and DNA Repair) and in one of two rats and one rabbit hepatocyte in vitroDNA repair studies. Additional in vivoand in vitrostudies using lymphoma cells, germinal cells, and fibroblasts from mice, bone marrow cells from Chinese hamsters and fibroblasts from human cell lines did not demonstrate any mutagenic potential for hydralazine.
The extent to which these findings indicate a risk to man is uncertain. While long-term clinical observation has not suggested that human cancer is associated with hydralazine use, epidemiologic studies have so far been insufficient to arrive at any conclusions.

Pregnancy

Teratogenic Effects

Pregnancy Category C

Animal studies indicate that hydralazine is teratogenic in mice at 20 to 30 times the maximum daily human dose of 200 to 300 mg and possibly in rabbits at 10 to 15 times the maximum daily human dose, but that it is nonteratogenic in rats. Teratogenic effects observed were cleft palate and malformations of facial and cranial bones.

There are no adequate and well-controlled studies in pregnant women. Although clinical experience does not include any positive evidence of adverse effects on the human fetus, hydralazine should be used during pregnancy only if the expected benefit justifies the potential risk to the fetus.

Nursing Mothers

Hydralazine has been shown to be excreted in breast milk.

Pediatric Use

Safety and effectiveness in pediatric patients have not been established in controlled clinical trials, although there is experience with the use of hydralazine in pediatric patients. The usual recommended oral starting dosage is 0.75 mg/kg of body weight daily in four divided doses. Dosage may be increased gradually over the next 3 to 4 weeks to a maximum of 7.5 mg/kg or 200 mg daily.

ADVERSE REACTIONS

Adverse reactions with hydralazine are usually reversible when dosage is reduced. However, in some cases it may be necessary to discontinue the drug. The following adverse reactions have been observed, but there has not been enough systematic collection of data to support an estimate of their frequency.

Common
headache, anorexia, nausea, vomiting, diarrhea, palpitations, tachycardia, angina pectoris.

Less Frequent
Digestive
constipation, paralytic ileus.
Cardiovascular
hypotension, paradoxical pressor response, edema.
Respiratory
dyspnea.
Neurologic
peripheral neuritis, evidenced by paresthesia, numbness, and tingling, dizziness; tremors; muscle cramps; psychotic reactions characterized by depression, disorientation, or anxiety.
Genitourinary
difficulty in urination.
Hematologic
blood dyscrasias, consisting of reduction in hemoglobin and red cell count, leukopenia, agranulocytosis, purpura, lymphadenopathy; splenomegaly.
Hypersensitive Reactions
rash, urticaria, pruritus, fever, chills, arthralgia, eosinophilia, and rarely, hepatitis.
Other
nasal congestion, flushing, lacrimation, conjunctivitis.

OVERDOSAGE

Acute Toxicity

No deaths due to acute poisoning have been reported. Highest known dose survived: adults, 10 g orally.
Oral LD50in rats: 173 and 187 mg/kg.

Signs and Symptoms

Signs and symptoms of overdosage include hypotension, tachycardia, headache, and generalized skin flushing.
Complications can include myocardial ischemia and subsequent myocardial infarction, cardiac arrhythmia, and profound shock.

Treatment

There is no specific antidote.

The gastric contents should be evacuated, taking adequate precautions against aspiration and for protection of the airway. An activated charcoal slurry may be instilled if conditions permit. These manipulations may have to be omitted or carried out after cardiovascular status has been stabilized, since they might precipitate cardiac arrhythmias or increase the depth of shock.

Support of the cardiovascular system is of primary importance. Shock should be treated with plasma expanders. If possible, vasopressors should not be given, but if a vasopressor is required, care should be taken not to precipitate or aggravate cardiac arrhythmia.

Tachycardia responds to beta blockers. Digitalization may be necessary, and renal function should be monitored and supported as required.

No experience has been reported with extracorporeal or peritoneal dialysis.

DOSAGE AND ADMINISTRATION

Initiate therapy in gradually increasing dosages; adjust according to individual response. Start with 10 mg four times daily for the first 2 to 4 days, increase to 25 mg four times daily for the balance of the first week. For the second and subsequent weeks, increase dosage to 50 mg four times daily. For maintenance, adjust dosage to the lowest effective levels.

The incidence of toxic reactions, particularly the L.E. cell syndrome, is high in the group of patients receiving large doses of hydralazine hydrochloride tablets.

In a few resistant patients, up to 300 mg of hydralazine hydrochloride tablets daily may be required for a significant antihypertensive effect. In such cases, a lower dosage of hydralazine hydrochloride tablets combined with a thiazide and/or reserpine or a beta blocker may be considered. However, when combining therapy, individual titration is essential to ensure the lowest possible therapeutic dose of each drug.

HOW SUPPLIED

Hydralazine Hydrochloride Tablets USP are available as:

10 mg Orange, round tablets debossed with SG on one side and 182 on other side. Available in Bottles of 100 (NDC 50228-182-01) and 1000 (NDC 50228-182-10).

25 mg Orange, round tablets debossed with SG on one side and 183 on other side. Available in Bottles of 100 (NDC 50228-183-01) and 1000 (NDC 50228-183-10).

50 mg Orange, round tablets debossed with SG on one side and 184 on other side. Available in Bottles of 100 (NDC 50228-184-01) and 1000 (NDC 50228-184-10).

100 mg Orange, round tablets debossed with SG on one side and 185 on other side. Available in Bottles of 100 (NDC 50228-185-01) and 1000 (NDC 50228-185-10).

Dispense in a tight, light-resistant container as defined in the USP, with a child-resistant closure (as required).

Store at 20° to 25° C (68° to 77° F); excursions permitted to 15° to 30° C (59° to 86° F). [See USP Controlled Room Temperature].

KEEP THIS AND ALL MEDICATIONS OUT OF THE REACH OF CHILDREN.

Manufactured by:
ScieGen Pharnaceuticals, Inc.
Hauppauge, NY 11788 USA

Rev: 1/2021